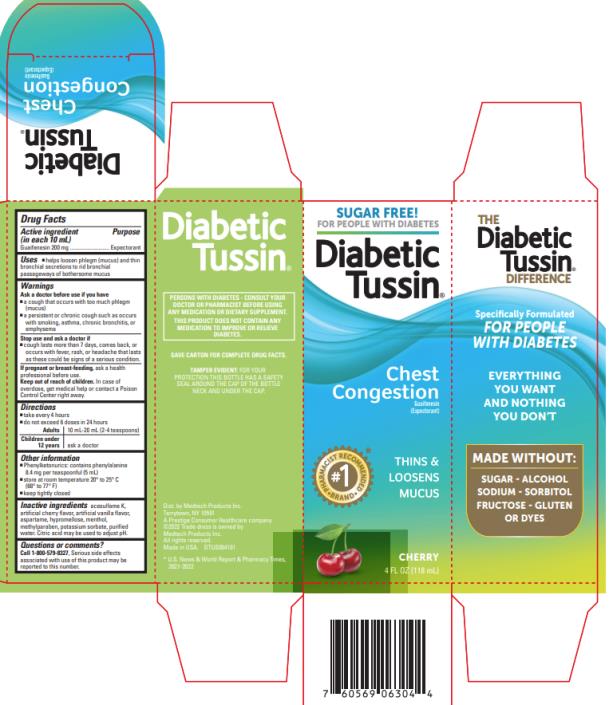 DRUG LABEL: Diabetic Tussin Expectorant
NDC: 61787-514 | Form: LIQUID
Manufacturer: MEDTECH PRODUCTS INC
Category: otc | Type: HUMAN OTC DRUG LABEL
Date: 20220307

ACTIVE INGREDIENTS: GUAIFENESIN 200 mg/10 mL
INACTIVE INGREDIENTS: ACESULFAME POTASSIUM; ASPARTAME; CHERRY; HYPROMELLOSE, UNSPECIFIED; MENTHOL, UNSPECIFIED FORM; METHYLPARABEN; POTASSIUM SORBATE; VANILLA; WATER; ANHYDROUS CITRIC ACID

Diabetic Tussin Expectorant 61787 514

DIABETIC TUSSIN EXPECTORANT- guaifenesin liquid
Medtech Products Inc., a Prestige Consumer Healthcare company

Disclaimer: Most OTC drugs are not reviewed and approved by FDA, however they may be marketed if they comply with applicable regulations and policies. FDA has not evaluated whether this product complies.

----------

Active ingredient (in each 10 mL)

Guaifenesin 200 mg

Purpose

Expectorant

Uses

- helps loosen phlegm (mucus) and thin bronchial secretions to rid bronchial passageways of bothersome mucus

Warnings

Ask a doctor before use if you have:

- a cough that occurs with too much phlegm (mucus)
- a persistent or chronic cough such as occurs with smoking, asthma, chronic bronchitis, or emphysema

Stop use and ask a doctor if:

- cough lasts more than 7 days, comes back, or occurs with fever, rash, or headache that lasts

These could be signs of a serious condition.

If pregnant or breast-feeding,

ask a health professional before use.

Keep out of reach of children.

In case of overdose, get medical help or contact a Poison Control Center right away.

Directions

- take every 4 hours
- do not exceed 6 doses in 24 hours

Adults | 10 mL - 20 mL (2 - 4 teaspoons)
Children under 12 years | ask a doctor

Other information

- Phenylketonurics: contains phenylalanine 8.4 mg per teaspoonful (5 mL)
- store at room temperature 20-25°C (68-77°F).
- keep tightly closed.

Inactive ingredients

Acesulfame K, artificial cherry flavor, artificial vanilla flavor, aspartame, hypromellose, menthol, methylparaben, potassium sorbate, purified water. Citric acid may be used to adjust pH.

Questions or comments?

Call 1-800-579-8327, serious side effects associated with use of this product may be reported to this number.

Rev #0514:00 04/19

Principal Display Panel

SUGAR & ALCOHOL FREE!

Specifically Formulated for Diabetics

Diabetic Tussin®

CHEST CONGESTION

Guaifenesin (Expectorant)

Thins & Loosens Mucus

4 FL OZ (118 mL)